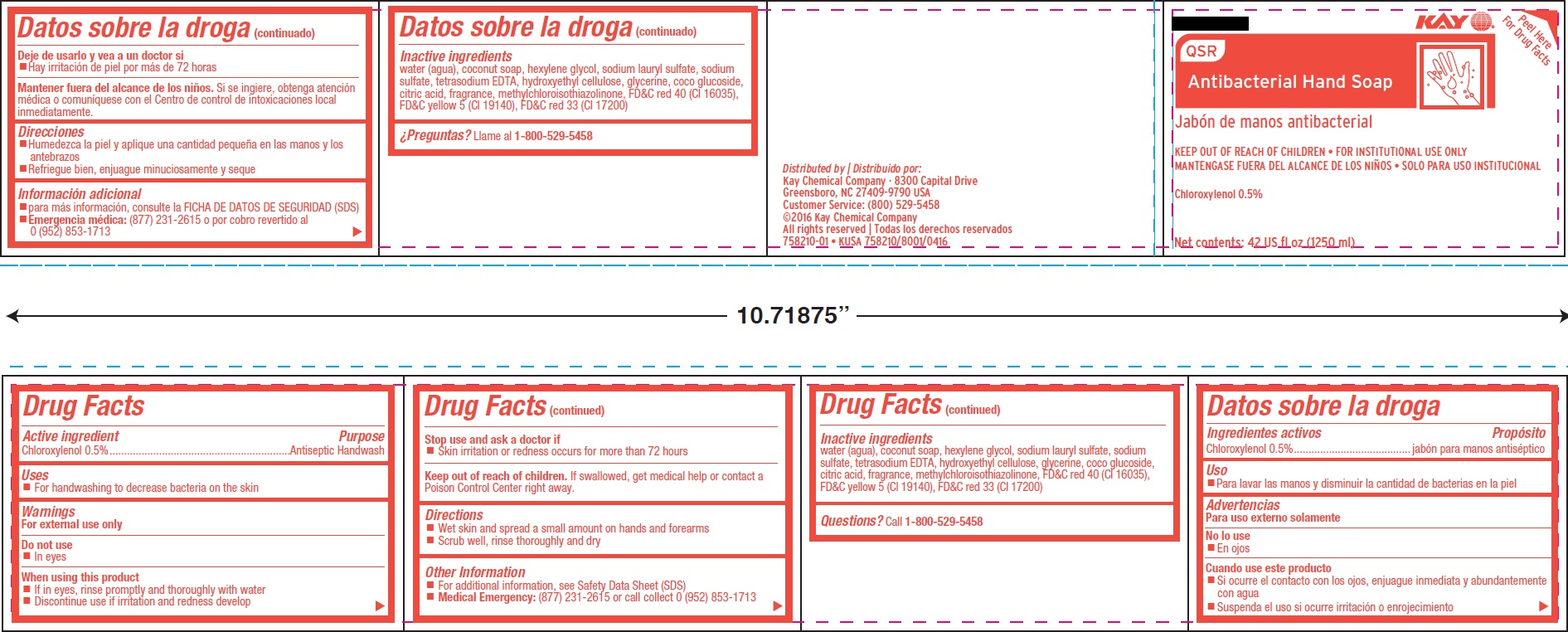 DRUG LABEL: Kay QSR Antibacterial Handsoap
NDC: 47593-671 | Form: SOLUTION
Manufacturer: Ecolab Inc.
Category: otc | Type: HUMAN OTC DRUG LABEL
Date: 20251217

ACTIVE INGREDIENTS: Chloroxylenol 5 mg/1 mL
INACTIVE INGREDIENTS: WATER; POTASSIUM COCOATE; HEXYLENE GLYCOL; SODIUM LAURYL SULFATE; SODIUM SULFATE ANHYDROUS; EDETATE SODIUM; HYDROXYETHYL CELLULOSE (3000 MPA.S AT 1%); GLYCERIN; COCO GLUCOSIDE; ANHYDROUS CITRIC ACID; METHYLCHLOROISOTHIAZOLINONE; FD&C RED NO. 40; FD&C YELLOW NO. 5; D&C RED NO. 33

Drug Facts

Active ingredient

Chloroxylenol, 0.5%

Purpose

Antiseptic handwash

Uses

- For handwashing to decrease bacteria on the skin.

Warnings

For external use only.

Do not use

- In eyes

When using this product

- If in eyes, rinse promptly and thoroughly with water
- Discontinue use if irritation and redness develop

Stop use and ask a doctor if

- Skin irritation or redness occurs for more than 72 hours

Keep out of reach of children. If swallowed, get medical help or contact a Poison Control Center right away.

Directions

- Wet skin and spread a small amount on hands and forearms
- Scrub well, rinse thoroughly and dry

Other Information

- For additional information, see Safety Data Sheet (SDS)
- Medical Emergency: (877) 231-2615 or call collect 0 (952) 853-1713.

Inactive ingredients

water (aqua), potassium cocoate, hexylene glycol, sodium sulfate, tetrasodium EDTA, sodium lauryl sulfate, hydroxyethylcellulose, glycerin, cocoglucoside, glyceryl oleate, citric acid, fragrance, methylchloroisothiazolinone, methylisothiazolinone, FD&C Red #40 (CI 16035), FD&C Yellow #5 (CI 19140), D&C Red #33 (CI 17200)

Questions? Call 1-800-529-5458

Principal display panel and representative label

Kay

QSR

Antibacterial Hand Soap

KEEP OUT OF REACH OF CHILDREN • FOR INSTITUTIONAL USE ONLY

Chloroxylenol 0.5%

Net Contents: 42 USA fl oz (1250 mL)

Distributed by:

Kay Chemical Company · 8300 Capital Drive

Greensboro, NC 27409-9790 USA

Customer Service: (800) 529-5458

©2016 Kay Chemical Company

All rights reserved

758210-01 • KUSA 758210/8001/0416